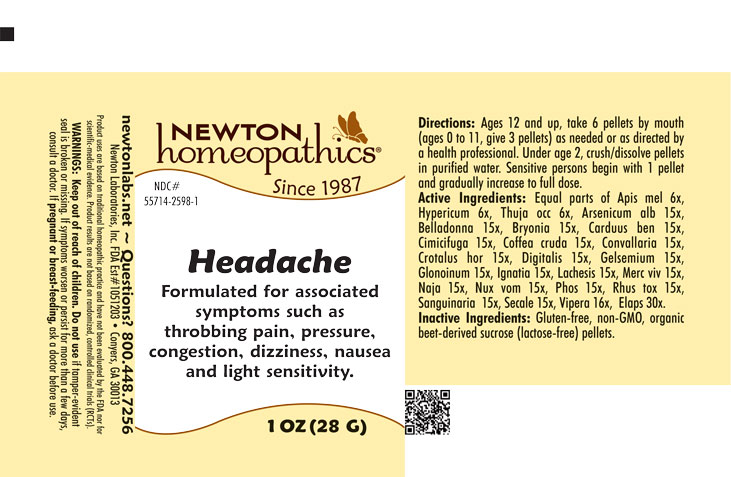 DRUG LABEL: Headache
NDC: 55714-2598 | Form: PELLET
Manufacturer: Newton Laboratories, Inc.
Category: homeopathic | Type: HUMAN OTC DRUG LABEL
Date: 20251202

ACTIVE INGREDIENTS: MICRURUS CORALLINUS VENOM 30 [hp_X]/1 g; ARSENIC TRIOXIDE 15 [hp_X]/1 g; ATROPA BELLADONNA 15 [hp_X]/1 g; BRYONIA ALBA ROOT 15 [hp_X]/1 g; CENTAUREA BENEDICTA 15 [hp_X]/1 g; BLACK COHOSH 15 [hp_X]/1 g; ARABICA COFFEE BEAN 15 [hp_X]/1 g; CONVALLARIA MAJALIS 15 [hp_X]/1 g; CROTALUS HORRIDUS HORRIDUS VENOM 15 [hp_X]/1 g; DIGITALIS 15 [hp_X]/1 g; GELSEMIUM SEMPERVIRENS ROOT 15 [hp_X]/1 g; NITROGLYCERIN 15 [hp_X]/1 g; STRYCHNOS IGNATII SEED 15 [hp_X]/1 g; LACHESIS MUTA VENOM 15 [hp_X]/1 g; MERCURY 15 [hp_X]/1 g; NAJA NAJA VENOM 15 [hp_X]/1 g; STRYCHNOS NUX-VOMICA SEED 15 [hp_X]/1 g; PHOSPHORUS 15 [hp_X]/1 g; TOXICODENDRON PUBESCENS LEAF 15 [hp_X]/1 g; SANGUINARIA CANADENSIS ROOT 15 [hp_X]/1 g; CLAVICEPS PURPUREA SCLEROTIUM 15 [hp_X]/1 g; VIPERA BERUS VENOM 16 [hp_X]/1 g; APIS MELLIFERA 6 [hp_X]/1 g; HYPERICUM PERFORATUM 6 [hp_X]/1 g; THUJA OCCIDENTALIS LEAFY TWIG 6 [hp_X]/1 g
INACTIVE INGREDIENTS: SUCROSE

Headache 2598P

INDICATIONS & USAGE SECTION

Formulated for associated symptoms such as throbbing pain, pressure, congestion, dizziness, nausea and light sensitivity.

DOSAGE & ADMINISTRATION SECTION

Directions: Ages 12 and up, take 6 pellets by mouth (ages 0 to 11, give 3 pellets) as needed or as directed by a health professional. Under age 2, crush/dissolve pellets in purified water. Sensitive persons begin with 1 pellet and gradually increase to full dose.

OTC - PURPOSE SECTION

Formulated for associated symptoms such as throbbing pain, pressure, congestion, dizziness, nausea and light sensitivity.

OTC - ACTIVE INGREDIENT SECTION

Equal parts of Apis mel. 6x, Hypericum 6x, Thuja occ 6x, Arsenicum alb 15x, Belladonna 15x, Bryonia 15x, Carduus ben 15x, Cimicifuga 15x, Coffea cruda 15x, Convallaria 15x, Crotalus hor 15x, Digitalis 15x, Gelsemium 15x, Glonoinum 15x, Ignatia 15x, Lachesis 15x, Merc viv 15x, Naja 15x, Nux vom 15x, Phos. 15x, Rhus tox 15x, Sanguinaria 15x, Secale 15x, Vipera 16x, Elaps 30x.

INACTIVE INGREDIENT SECTION

Inactive Ingredients: Gluten-free, non-GMO, organic beet-derived sucrose (lactose-free) pellets.

QUESTIONS SECTION

newtonlabs.net - Questions? 800.448.7256

Newton Laboratories, Inc. FDA Est # 1051203 Conyers, GA 30013

OTC - PREGNANCY OR BREAST FEEDING SECTION

If pregnant or breast-feeding, ask a doctor before use.

WARNINGS SECTION

WARNINGS: Keep out of reach of children. Do not use if tamper-evident seal is broken or missing. If symptoms worsen or persist for more than a few days, consult a doctor. If pregnant or breast-feeding, ask a doctor before use.

OTC - KEEP OUT OF REACH OF CHILDREN SECTION

Keep out of reach of children